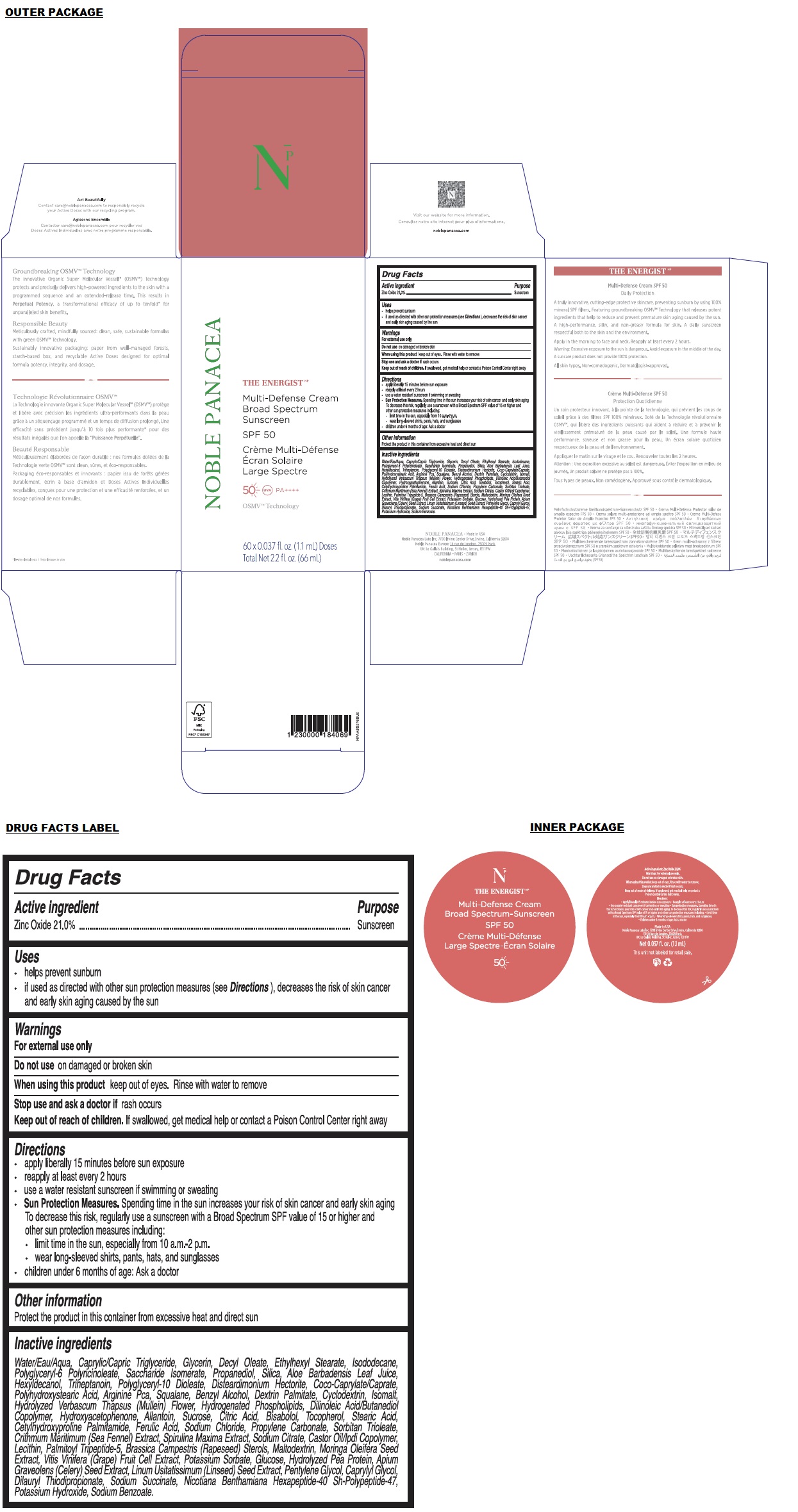 DRUG LABEL: THE ENERGIST Multi-Defense Broad Spectrum Sunscreen SPF 50
NDC: 83637-150 | Form: CREAM
Manufacturer: Noble Panacea Labs, Inc.
Category: otc | Type: HUMAN OTC DRUG LABEL
Date: 20260116

ACTIVE INGREDIENTS: ZINC OXIDE 21 g/100 mL
INACTIVE INGREDIENTS: WATER; MEDIUM-CHAIN TRIGLYCERIDES; GLYCERIN; DECYL OLEATE; ETHYLHEXYL STEARATE; ISODODECANE; POLYGLYCERYL-6 POLYRICINOLEATE; SACCHARIDE ISOMERATE; PROPANEDIOL; SILICON DIOXIDE; ALOE VERA LEAF; HEXYLDECANOL; TRIHEPTANOIN; POLYGLYCERYL-10 DIOLEATE; DISTEARDIMONIUM HECTORITE; COCOYL CAPRYLOCAPRATE; POLYHYDROXYSTEARIC ACID (2300 MW); ARGININE PIDOLATE; SQUALANE; BENZYL ALCOHOL; DEXTRIN PALMITATE (CORN; 20000 MW); CYCLODEXTRINS; ISOMALT; VERBASCUM THAPSUS FLOWER; LECITHIN, SUNFLOWER; DILINOLEIC ACID/BUTANEDIOL COPOLYMER; HYDROXYACETOPHENONE; ALLANTOIN; SUCROSE; CITRIC ACID MONOHYDRATE; LEVOMENOL; TOCOPHEROL; STEARIC ACID; CETYLHYDROXYPROLINE PALMITAMIDE; FERULIC ACID; SODIUM CHLORIDE; PROPYLENE CARBONATE; SORBITAN TRIOLEATE; CRITHMUM MARITIMUM WHOLE; ARTHROSPIRA MAXIMA; SODIUM CITRATE, UNSPECIFIED FORM; DIOCTYLDODECYL ISOPHORONE DIISOCYANATE; PALMITOYL TRIPEPTIDE-5; RAPESEED STEROL; MALTODEXTRIN; MORINGA OLEIFERA SEED; PEA PROTEIN; VITIS VINIFERA HIGH TANNIN CULTIVAR FRUIT CELL LYSATE; POTASSIUM SORBATE; ANHYDROUS DEXTROSE; CELERY SEED; FLAX SEED; PENTYLENE GLYCOL; CAPRYLYL GLYCOL; DILAURYL THIODIPROPIONATE; SODIUM SUCCINATE HEXAHYDRATE; NICOTIANA BENTHAMIANA WHOLE; POTASSIUM HYDROXIDE; SODIUM BENZOATE

THE ENERGISTNP Multi-Defense Broad Spectrum Sunscreen SPF 50

Active ingredient

Zinc Oxide 21.0%

Purpose

Sunscreen

Uses

• helps prevent sunburn
• if used as directed with other sun protection measures (see Directions), decreases the risk of skin cancer and early skin aging caused by the sun

Warnings

For external use only

Do not useon damaged or broken skin

When using this productkeep out of eyes. Rinse with water to remove

Stop use and ask a doctor ifrash occurs

Keep out of reach of children. If swallowed, get medical help or contact a Poison Control Center right away

Directions

• apply liberally 15 minutes before sun exposure
• reapply at least every 2 hours
• use a water resistant sunscreen if swimming or sweating
• Sun Protection Measures.Spending time in the sun increases your risk of skin cancer and early skin aging. To decrease this risk, regularly use a sunscreen with a Broad Spectrum SPF value of 15 or higher and other sun protection measures including:
• limit time in the sun, especially from 10 a.m.-2 p.m.
• wear long-sleeved shirts, pants, hats, and sunglasses
• children under 6 months of age: Ask a doctor

Other information

Protect the product in this container from excessive heat and direct sun

Inactive ingredients

Water/Eau/Aqua, Caprylic/Capric Triglyceride, Glycerin, Decyl Oleate, Ethylhexyl Stearate, Isododecane, Polyglyceryl-6 Polyricinoleate, Saccharide Isomerate, Propanediol, Silica, Aloe Barbadensis Leaf Juice, Hexyldecanol, Triheptanoin, Polyglyceryl-10 Dioleate, Disteardimonium Hectorite, Coco-Caprylate/Caprate, Polyhydroxystearic Acid, Arginine Pca, Squalane, Benzyl Alcohol, Dextrin Palmitate, Cyclodextrin, Isomalt, Hydrolyzed Verbascum Thapsus (Mullein) Flower, Hydrogenated Phospholipids, Dilinoleic Acid/Butanediol Copolymer, Hydroxyacetophenone, Allantoin, Sucrose, Citric Acid, Bisabolol, Tocopherol, Stearic Acid, Cetylhydroxyproline Palmitamide, Ferulic Acid, Sodium Chloride, Propylene Carbonate, Sorbitan Trioleate, Crithmum Maritimum (Sea Fennel) Extract, Spirulina Maxima Extract, Sodium Citrate, Castor Oil/Ipdi Copolymer, Lecithin, Palmitoyl Tripeptide-5, Brassica Campestris (Rapeseed) Sterols, Maltodextrin, Moringa Oleifera Seed Extract, Vitis Vinifera (Grape) Fruit Cell Extract, Potassium Sorbate, Glucose, Hydrolyzed Pea Protein, Apium Graveolens (Celery) Seed Extract, Linum Usitatissimum (Linseed) Seed Extract, Pentylene Glycol, Caprylyl Glycol, Dilauryl Thiodipropionate, Sodium Succinate, Nicotiana Benthamiana Hexapeptide-40 sh-Polypeptide-47, Potassium Hydroxide, Sodium Benzoate.

UVA PA++++

Refill / Recharge

OSMV™ Technology

NOBLE PANACEA - Made in USA
Noble Panacea Labs Inc, 7700 Irvine Center Drive, Irvine, California 92618
Noble Panacea Europe: 18 rue de Londres, 75009 Paris
UK: Le Gallais Building, St Helier, Jersey, JE1 1FW
CALIFORNIA - PARIS - ZURICH

Daily Protection

A truly innovative, cutting-edge protective skincare, preventing sunburn by using 100% mineral SPF filters. Featuring groundbreaking OSMV™ Technology that releases potent ingredients that help to reduce and prevent premature skin aging caused by the sun. A high-performance, silky, and non-greasy formula for skin. A daily sunscreen respectful both to the skin and the environment.

Apply in the morning to face and neck. Reapply at least every 2 hours.

Warning: Excessive exposure to the sun is dangerous. Avoid exposure in the middle of the day.

A suncare product does not provide 100% protection.

All skin types. Non-comedogenic. Dermatologist-approved.

Groundbreaking OSMV™ Technology
The innovative Organic Super Molecular Vessel™ (OSMV™) Technology protects and precisely delivers high-powered ingredients to the skin with a programmed sequence and an extended-release time. This results in Perpetual Potency, a transformational efficacy of up to tenfold* for unparalleled skin benefits.

Refill your octagonal box with the 60 Active Dose Refill.

Responsible Beauty
Meticulously crafted, mindfully sourced: clean, safe, sustainable formulas with green OSMV™ Technology.

Sustainably innovative packaging: paper from well-managed forests, starch-based box, and recyclable Active Doses designed for optimal
formula potency, integrity, and dosage.

* In-vitro clinical tests

Act Beautifully
Contact care@noblepanacea.com to responsibly recycle your Active Doses with our recycling program.

Visit our website for more information.

noblepanacea.com